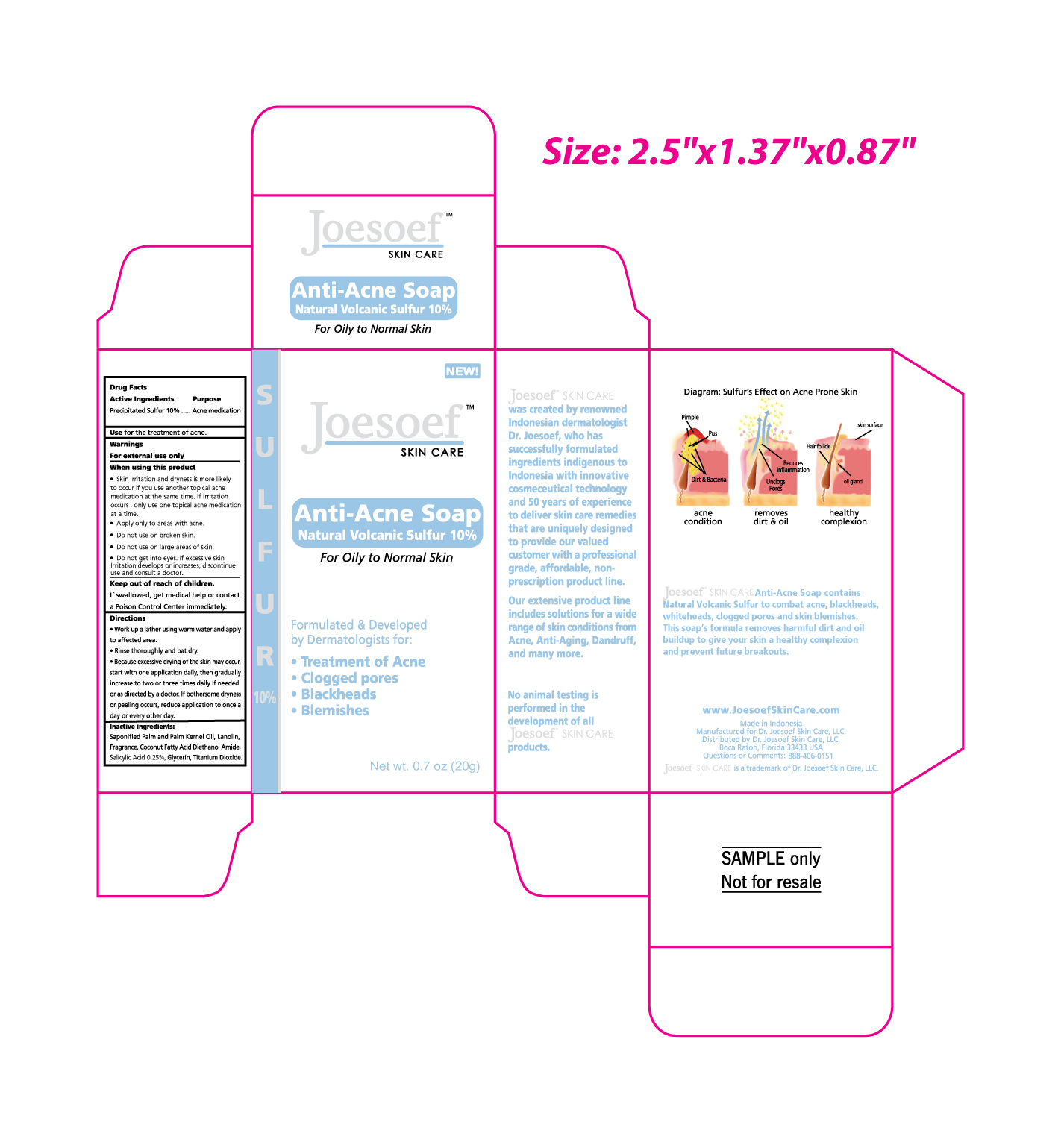 DRUG LABEL: Anti Acne Natural Volcanic Sulfur
NDC: 26050-101 | Form: SOAP
Manufacturer: PT. GALENIUM PHARMASIA LABORATORIES
Category: otc | Type: HUMAN OTC DRUG LABEL
Date: 20250123

ACTIVE INGREDIENTS: SULFUR 10 g/100 g
INACTIVE INGREDIENTS: SALICYLIC ACID; PALM KERNEL OIL; LANOLIN; COCO DIETHANOLAMIDE; GLYCERIN; TITANIUM DIOXIDE

Anti-Acne Soap Natural Volcanic Sulfur 10%

Drug Facts

Active Ingredients

Precipitated Sulfur 10%

Purpose

Acne medication

Use

for the treatment of acne.

Warnings

For external use only

When using this product

- Skin irritation and dryness is more likely to occur if you use another topical acne medication at the same time. If irritation occurs , only use one topical acne medication at a time.
- Apply only to areas with acne.

- Do not use on broken skin.
- Do not use on large areas of skin.
- Do not get into eyes. If excessive skin Irritation develops or increases, discontinue use and consult a doctor.

Keep out of reach of children.

If swallowed, get medical help or contact a Poison Control Center immediately.

Directions

- Work up a lather using warm water and apply to affected area.
- Rinse thoroughly and pat dry.
- Because excessive drying of the skin may occur, start with one application daily, then gradually increase to two or three times daily if needed or as directed by a doctor. If bothersome dryness or peeling occurs, reduce application to once a day or every other day.

Inactive ingredients

Saponified Palm and Palm Kernel Oil, Lanolin, Fragrance, Coconut Fatty Acid Diethanol Amide, Salicylic Acid 0.25%, Glycerin, Titanium Dioxide.

Questions or Comments

888-406-0151

Distributed by Dr. Joesoef Skin Care, LLC.
Boca Raton, Florida 33433 USA

PRINCIPAL DISPLAY PANEL - 20 g Box

SULFUR 10%

NEW!

Joesoef™
SKIN CARE

Anti-Acne Soap
Natural Volcanic Sulfur 10%

For Oily to Normal Skin

Formulated & Developed
by Dermatologists for:

• Treatment of Acne
• Clogged pores
• Blackheads
• Blemishes

Net wt. 0.7 oz (20g)